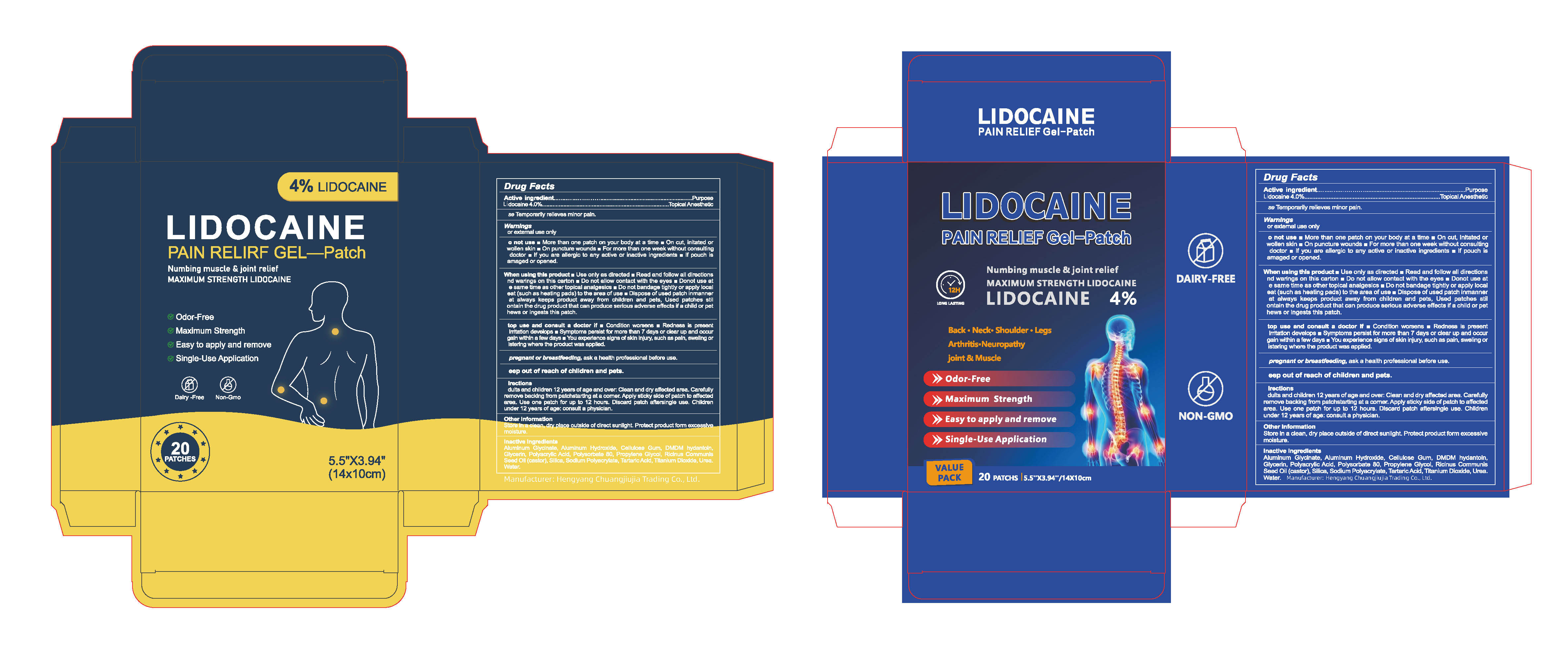 DRUG LABEL: 4% Lidocaine Patch
NDC: 84735-010 | Form: PATCH
Manufacturer: Hengyang Chuangjiujia Trading Co., Ltd.
Category: otc | Type: HUMAN OTC DRUG LABEL
Date: 20251106

ACTIVE INGREDIENTS: LIDOCAINE 0.04 g/1 1
INACTIVE INGREDIENTS: ALUMINUM GLYCINATE; POLYACRYLIC ACID (250000 MW); WATER; ALUMINUM HYDROXIDE; CELLULOSE GUM; TARTARIC ACID; TITANIUM DIOXIDE; DMDM HYDANTOIN; SILICA; UREA; RICINUS COMMUNIS (CASTOR) SEED OIL; SODIUM POLYACRYLATE (2500000 MW); GLYCERIN; POLYSORBATE 80; PROPYLENE GLYCOL

84735-010 4% Lidocaine Patch

ACTIVE INGREDIENT

Lidocaine 4%

PURPOSE

Topical Aneslhetic

INDICATIONS AND USAGE

Use Temperarily relicwes miner pain.

WARNINGS

For external use only

Do not use More than one patch on your body at a time On gut, initated orswollen gkin On puncture wounds For more than one week without consultinga doctor if you are allergic to any aclive or inactive ingrediantsm lf pouch iscambged or opred.

When using this product Use only as directed Read and follow all directionsand warings on this carton Do not allow oontact with the oyes Do not use atthe same lime as oler bopical analgesics Do nat bandage lighlly or apoly localheat (such as heating pads, to the area of use Dispose of uged patch inmannerihat always keeps product away irom children and pots, Lised paiches siilcontain the drug product that can produce gerious adverge elfecis if a child or petchaws or ingasis ihis patchh.

Stop use and consult a doctor if condtion worsensm Redness is presert lniation develops Sympioms persist for more than 7 dlays or clear up and oocuragain willin a ferw darys You coperienoe signs of skin injury, such as pain, sweling or bllslering where the product was applled.

Keep out of reach of children and pets.

DOSAGE AND ADMINISTRATION

Adults and chldren 12 years of age and over: Clean and dry affected areaCarefully remove backing from patchstarting at a corner. Apply sticky sideof patch to affected area. Use one patch for up to 12 hours. Discard patchaftersingle use. Children under 12 years of age: consult a physician.

INACTIVE INGREDIENT

Aluminum Glycinate
Aluminum Hydroxide
Cellulose Gum (Sodium CMC)
DMDM Hydantoin
Glycerin
Polyacrylic Acid
Polysorbate 80
Propylene Glycol
Ricinus Communis (Castor) Seed Oil
Silica (Colloidal)
Sodium Polyacrylate
Tartaric Acid
Titanium Dioxide
Urea
Water (Purified Water)